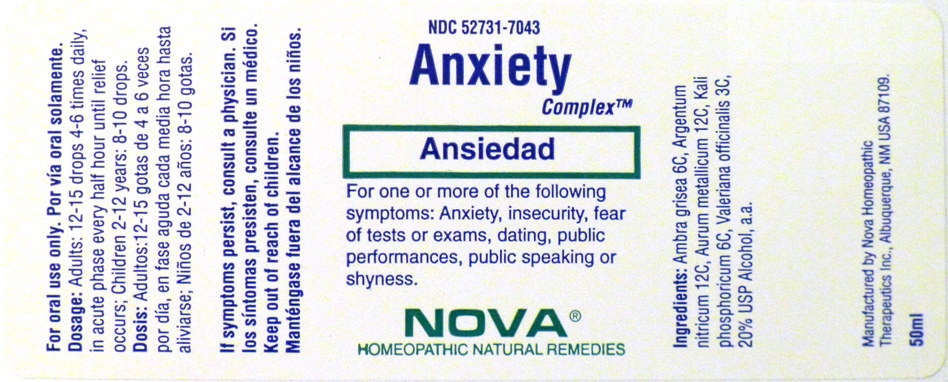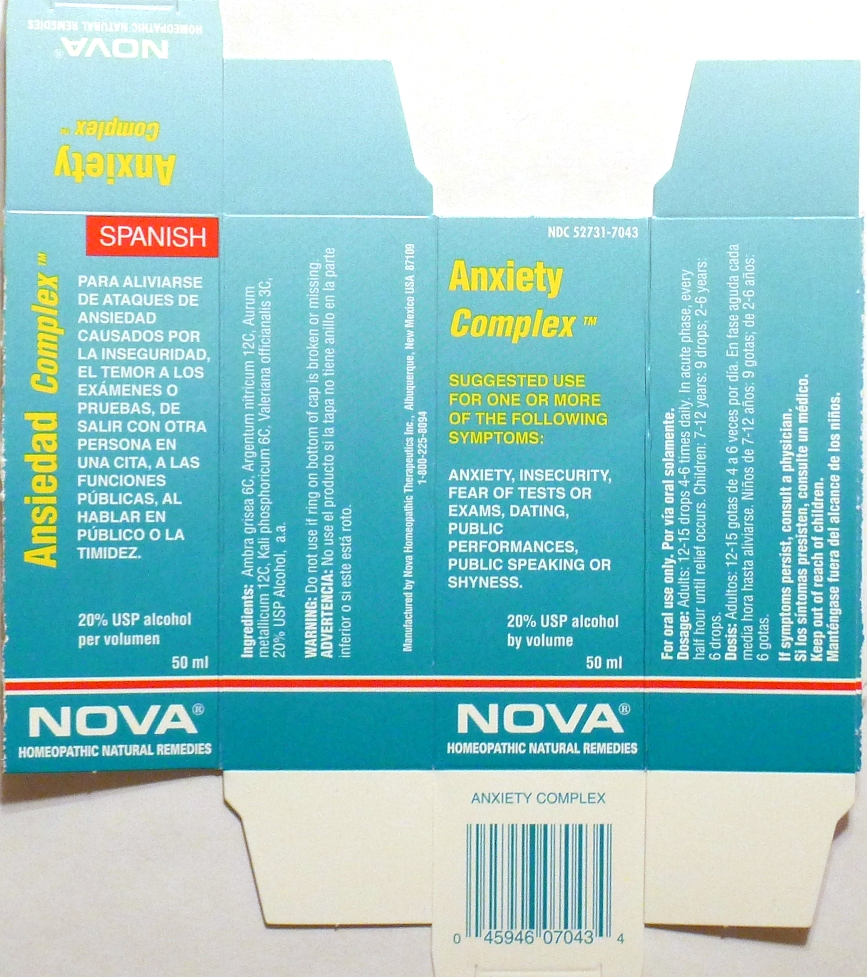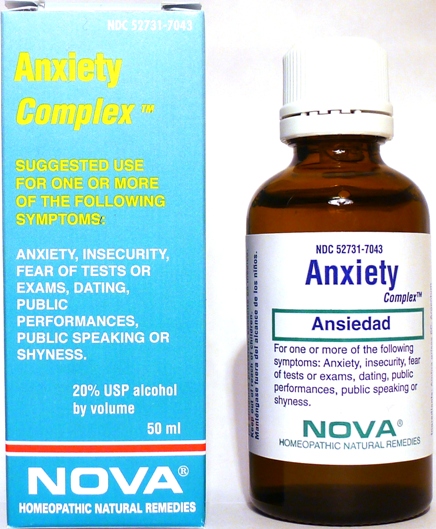 DRUG LABEL: Anxiety Complex
NDC: 52731-7043 | Form: LIQUID
Manufacturer: Nova Homeopathic Therapeutics, Inc.
Category: homeopathic | Type: HUMAN OTC DRUG LABEL
Date: 20110601

ACTIVE INGREDIENTS: AMBERGRIS 6 [hp_C]/1 mL; SILVER NITRATE 12 [hp_C]/1 mL; GOLD 12 [hp_C]/1 mL; POTASSIUM PHOSPHATE, DIBASIC 6 [hp_C]/1 mL; VALERIAN 3 [hp_C]/1 mL
INACTIVE INGREDIENTS: ALCOHOL

Anxiety Complex

Purpose:

Suggested use for one or more of the following symptoms:

Anxiety, insecurity, fear of tests or exams, dating, public performances, public speaking or shyness.

Usage and Dosage:

For oral use only.

DOSAGE AND ADMINISTRATION

Adults:
In Acute Phase:
12-15 drops, every half hour until relief occurs
When Relief Occurs:
12-15 drops, 4-6 times per day
Children 2-12 years:
8-10 drops, 4-6 times per day

Infants 0-24 months:
3 drops, 4-6 times per day

Warnings:

Keep out of reach of children.

WARNINGS

If symptoms persist, consult a physician.
Do not use if ring on bottom of cap is broken or missing.

Active Ingredients:

Ambra grisea 6C, Argentum nitricum 12C, Aurum metallicum 12C, Kali phosphoricum 6C, Valeriana officianalis 3C

Inactive Ingredients:

Alcohol, 20% USP

QUESTIONS

Manufactured by Nova Homeopathic Therapeutics Inc., Albuquerque, New Mexico USA 87109
1-800-225-8094

PACKAGE LABEL

Anxiety Complex Product

Anxiety Complex Bottle Label

Anxiety Complex Box